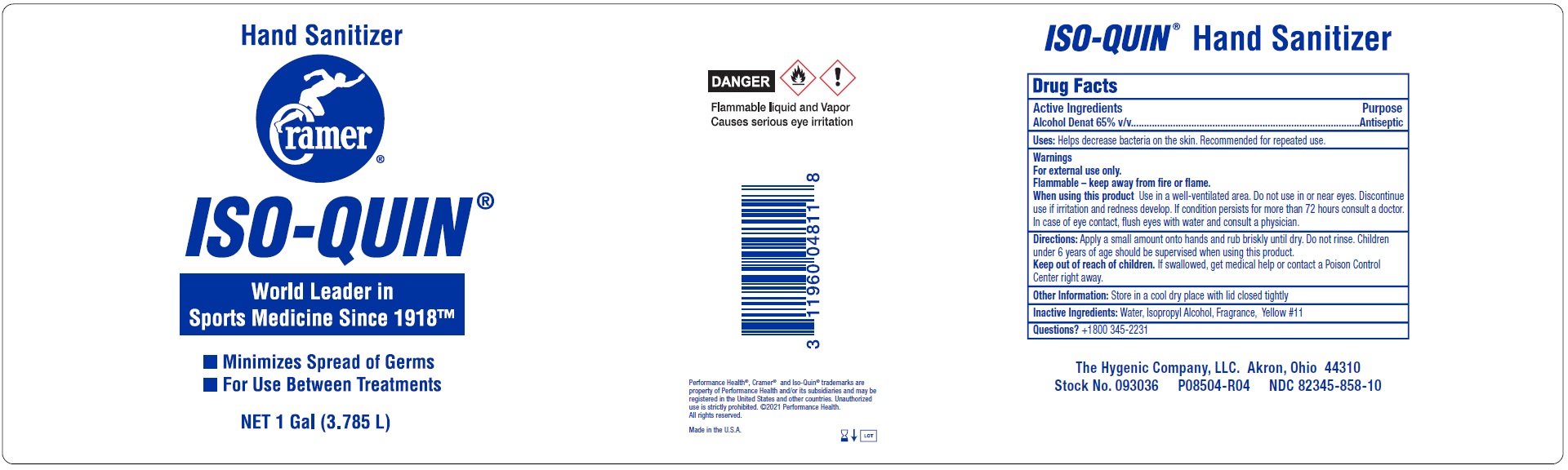 DRUG LABEL: Iso-Quin hand sanitizer
NDC: 82345-858 | Form: LIQUID
Manufacturer: The Hygenic Company, LLC.
Category: otc | Type: HUMAN OTC DRUG LABEL
Date: 20231105

ACTIVE INGREDIENTS: ALCOHOL 65 mL/100 mL
INACTIVE INGREDIENTS: WATER; ISOPROPYL ALCOHOL; D&C YELLOW NO. 11

Iso-Quin hand sanitizer

Active Ingredients

Alcohol Denat 65% v/v

Purpose

Antiseptic

Uses:

Helps decrease bacteria on the skin. Recommended for repeated use.

Warnings

For external use only.

Flammable - keep away from fire or flame.

When using this product

Use in a well-ventilated area. Do not use in or near eyes. Discontinue use if irritation and redness develop. If condition persists for more than 72 hours consult a doctor. In case of eye contact, flush eyes with water and consult a physician.

Keep out of reach of children.

If swallowed, get medical help or contact a Poison Control Center right away.

Directions:

Apply a small amount onto hands and rub briskly until dry. Do not rinse. Children under 6 years of age should be supervised when using this product.

Other Information:

Store in a cool dry place with lid closed tightly

Inactive Ingredients:

Water, Isopropyl Alcohol, Fragrance, Yellow #11

Questions?

+1800 345-2231